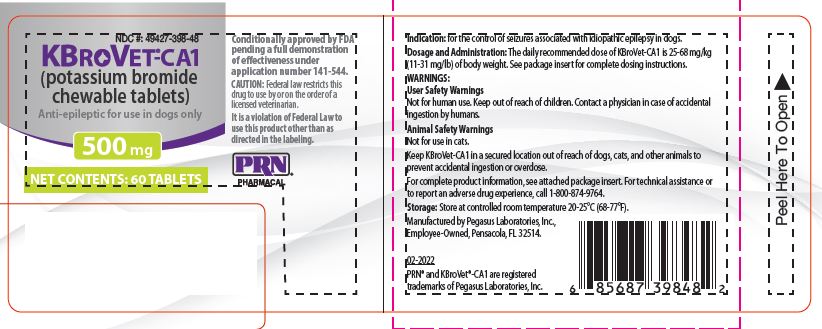 DRUG LABEL: KBroVet-CA1 500
NDC: 49427-398 | Form: TABLET, CHEWABLE
Manufacturer: Pegasus Laboratories, Inc.
Category: animal | Type: PRESCRIPTION ANIMAL DRUG LABEL
Date: 20250812

ACTIVE INGREDIENTS: POTASSIUM BROMIDE 500 mg/1 1
INACTIVE INGREDIENTS: CELLULOSE, MICROCRYSTALLINE 385.7 mg/1 1; DIBASIC CALCIUM PHOSPHATE DIHYDRATE 266 mg/1 1; STEARIC ACID 121 mg/1 1

KBroVet®-CA1 (potassium bromide chewable tablets)

Anti-epileptic for use in dogs only.

Conditionally approved by FDA pending a full demonstration of effectiveness under application number 141-544.

CAUTION:

Federal law restricts this drug to use by or on the order of a licensed veterinarian. Use only as directed. It is a violation of Federal Law to use this product other than as directed in the labeling.

CONTRAINDICATIONS:

KBroVet-CA1 should not be used in animals with a history of hypersensitivity to bromide.

DESCRIPTION:

KBroVet-CA1 are flavored chewable tablets that contain potassium bromide (KBr). KBr is an odorless, colorless crystal or white crystalline powder or white granular solid with a pungent bitter saline taste. The molar mass of KBr is 119.002 g/mol, with a high soluability in water, glycerol and ethanol.

INDICATION:

KBroVet-CA1 (potassium bromide chewable tablets) are indicated for the control of seizures associated with idiopathic epilepsy in dogs.

DOSAGE AND ADMINISTRATION:

The total recommended daily dosage range for oral administration is 25 - 68 mg/kg (11-31 mg/lb) of body weight. The dosage of KBroVet-CA1 should be adjusted based on monitoring of clinical response of the individual patient. KBroVet-CA1 may be dosed with or without food. Use of an initial loading dosage regimen may be considered on an individual patient basis, balancing the time required to achieve a therapeutic response while minimizing side effects.

WARNINGS: User Safety Warnings

Not for human use. Keep out of reach of children. Contact a physician in case of accidental ingestion by humans.

Animal Safety Warnings

Not for use in cats.

Keep KBroVet-CA1 in a secured location out of reach of dogs, cats, and other animals to prevent accidental ingestion or overdose.

PRECAUTIONS:

Dogs receiving KBr should be carefully monitored when changing diets, administering chloride-containing IV fluids, and administering concurrent medications. Careful monitoring is important in dogs that have a condition that may cause difficulty maintaining electrolyte balance.

Animals with decreased renal function may be predisposed to bromide toxicosis.

Some dogs may experience epileptic episodes that are unresponsive or refractory to KBr monotherapy and KBr alone may not be adequate treatment for every dog with idiopathic epilepsy.

The safe use of KBroVet-CA1 has not been evaluated in dogs that are intended for breeding, or that are pregnant or lactating. The safe use of KBr in neonates and young animals has not been established. Reproductive effects of KBr have been reported in other species. In dogs, ataxia, diarrhea, hematochezia, excessive salivation, shivering, skin lesions, stupor progressing to coma and death have been reported with a dose of 200 to 500 mg/kg a day for 4 to 26 weeks.

ADVERSE REACTIONS:

In a retrospective field study of 51 dogs diagnosed with idio- pathic epilepsy and receiving only KBr to control seizures associated with idiopathic epilepsy, adverse reactions were documented for the initial 60 days of treatment. Increased appetite, weight gain, vomiting/regurgitation and sedation were the most common clinical abnormalities documented in the 60 day period after start of KBr therapy (Table 1).

Table 1. Adverse Reactions Reported During Initial Dosing Phase (60 Day Period After Start of KBr Therapy)

Adverse Reaction | Number of Dogs with the; Adverse Reaction
Increased Appetite | 11
Weight Gain | 8
Vomiting | 5
Regurgitation | 4
Sedation | 3
Polydipsia | 2
Ataxia | 2
Polyuria | 2
Weakness | 2
Decreased Activity | 1
Diarrhea | 1
Disorientation | 1
Lethargy | 1
Partial Lack of Efficacy | 1
Petit Mal Epilepsy | 1
Seizure | 1
Tiredness | 1
Tremors | 1

Adverse reactions were also documented during the 30 days prior to KBr sample submission. Weight gain, weakness, ataxia, and increased appetite were the most common adverse reactions documented during this time period (Table 2).

Table 2. Adverse Reactions Reported During Dosing Phase (30 Day Period Before KBr Sample Submission)

Adverse Reaction | Number of Dogs with the; Adverse Reaction
Weight Gain | 7
Weakness | 5
Ataxia | 4
Increased Appetite | 4
Polydipsia | 3
Sedation | 3
Diarrhea | 2
Polyuria | 2
Regurgitation | 2
Vomiting | 2
Decreased Appetite | 1
Disorientation | 1
Loose Stool | 1
Panting | 1
Tremors | 1

Adverse events associated with concurrent use of KBr with other antiepileptic drugs such as phenobarbital have been reported. Neurologic signs were the most common adverse event and included sedation, irritability, restlessness, depres- sion, behavioral changes, ataxia, hind limb paresis, mydriasis, stupor, and coma. The neurologic signs were reported to be reversible.

CONTACT INFORMATION:

For a copy of the Safety Data Sheet (SDS) or to report suspected adverse drug events, contact Pegasus Laboratories at 1-800-874-9764. For additional information reporting adverse drug experience reporting for animal drugs, contact FDA at 1-888-FDA-VETS or www.fda.gov/reportanimalae.

CLINICAL PHARMACOLOGY

Mechanism of action: KBr is a halide salt that is thought to exert its antiepileptic activity by passing through neuronal chloride ion channels, thereby hyperpolarizing neuronal membranes, raising the seizure threshold, and stabilizing neurons against excitatory input from epileptic foci.

Pharmacokinetics: The pharmacokinetics of a multi-dose regimen of administration in normal dogs have been evaluated as described in a comprehensive literature review. In one study, KBr was administered at 30 mg/kg orally every 12 hrs for a period of 115 days. Serum, urine, and cerebrospinal fluid (CSF) bromide concentrations were measured at the onset of dosing, during the accumulation phase, at steady-state, and after a subsequent dose adjustment. Median elimination half-life and steady-state serum concen- tration were 15.2 days and 245 mg/dL, respectively. Apparent total body clearance was 16.4 mL/day/kg and volume of distribution was 0.40 L/kg. The CSF:serum bromide ratio at steady-state was 0.77.

Distribution, Metabolism, and Elimination: Bromide distributes into the CSF and interstitial tissues of the brain and is actively transported out of the CNS via the choroid plexus. At pharmacological doses, the active transport mechanism is overwhelmed and bromide accumulates in the brain and CSF. Bromide is not metabolized by the liver and is eliminated unchanged, primarily by renal clearance. Increased dietary consumption of chloride can promote loss of bromide in the urine, leading to a lowering of serum bromide concentrations. Decreased chloride consumption will promote increased renal reabsorption of bromide, causing an increase in bromide elimination half-life in dogs.

REASONABLE EXPECTATION OF EFFECTIVENESS:

KBroVet-CA1 is conditionally approved pending a full demonstration of effectiveness.

Additional information for Conditional Approvals can be found by searching www.fda.gov for “animal conditional approval”.

Two retrospective studies were used to determine the dose and demonstrate a reasonable expectation of effectiveness for KBroVet-CA1 for the control of seizures associated with idiopathic epilepsy in dogs.

In a dose determination retrospective study, the total daily oral dose of KBr given for greater than or equal to 45 days (approaching steady- state conditions) was described. To be included in this study, cases were required to meet the following eligibility require- ments: samples submitted for serum bromide concentration evaluation within the required date range (January 1, 2003 to August 31, 2010), and dogs were between greater than or equal to 0.5 and less than or equal to 5.0 years of age, receiving only KBr to control seizures associated with idiopathic epilepsy, administered KBr once or twice daily for greater than or equal to 45 days at the dose noted on the submission form, and the serum bromide concentration was greater than or equal to 0.8 and less than or equal to 3.5 mg/mL.

A total of 284 case records (58.5% male and 41.6% female), with a mean age of 3.6 years (0.7-5.0 years) and a mean body weight of 20.5 kg (1.3-88.2 kg), were evaluated between January 1, 2003 to August 31, 2010. The mean total daily oral dose was 46.6 (±21.9) mg/kg with a range of 24.5-68.3 mg/kg. These results describe the total daily oral dose range to achieve serum bromide concentrations within 10% of the published therapeutic range (greater than or equal to 0.8 and less than or equal to 3.5 mg/mL)1,2 for dogs with idiopathic epilepsy.

A pilot retrospective study involving review of case records of 51 client-owned dogs was conducted to evaluate the effec- tiveness of KBr in dogs. This retrospective study evaluated case records of dogs previously receiving only KBr to control seizures associated with idiopathic epilepsy and for which blood samples had been analyzed to quantify serum bromide concentrations for the purpose of therapeutic drug monitoring.

Seizure counts, seizure count changes, seizure event days per month and seizure severity scores were tabulated for eligible cases, comparing the 30 day period before initial treatment with KBr and the 30 day period of steady state KBr dosing. Seizure count within an individual case was required to decrease by 50% or greater in order for the case to be classified as a seizure count success. Similarly, reduction in the number of seizure event days per month by greater than or equal to 50% was required for the case to be classified as a seizure event day count success. No increase in severity score denoted an individual case treatment success for this variable. Of the 51 evaluable cases, 27 were determined as valid for safety and effectiveness data and 24 were determined to be valid for only safety data.

Of the 27 cases, 19 (70%) were defined as “success” and 8 (30%) were defined as “failures” based on seizure count results. Eighteen (67%) were defined as “success” and 9 (33%) were defined as “failures” based on seizure event day results. Seizure severity score decreased or did not change in 25 of the 27 cases evaluated for effectiveness. Overall, of the 27 dogs included in the effectiveness analysis, 18 (67%) were considered treatment successes and 9 (33%) were considered treatment failures.

ANIMAL SAFETY:

Safety was assessed in a systematic review of literature and a retrospective field study. Reversible neurologic signs were the most consistently reported adverse effect and were generally associated with adjunctive KBr treatment or high serum bromide concentrations. Adverse effects were also seen in some dogs with low serum bromide concentration. Dermatologic and respiratory abnormalities were rare in dogs. Evidence suggested that administration of KBr with food may alleviate gastrointestinal irritation and that monitoring for polyphagia, thyroid hormone abnormalities, and high serum bromide concentrations may be beneficial.

HOW SUPPLIED:

KBroVet-CA1 are flavored, non-scored tablets containing
250 mg or 500 mg of potassium bromide per tablet. KBroVet-CA1 is packaged in bottles containing 60 or 180 tablets.

500 mg Tablet (60 ct) bottle NDC 49427-398-48

250 mg Tablet (60 ct) bottle NDC 49427-397-48

500 mg Tablet (180 ct) bottle NDC 49427-398-50

250 mg Tablet (180 ct) bottle NDC 49427-397-50

STORAGE CONDITIONS:

Store at controlled room temperature 20-25°C (68-77°F).

Keep out of reach of children and animals.

REFERENCES

^1Boothe DM. Anticonvulsant and other neurologic therapies. In: Boothe DM, Ed. SmallAnimal clinical pharmacology and therapeutics. Philadelphia: WB Saunders Co.,2001; 431-456

^2Dewey CW. Anticonvulsant therapy in dogs and cats. Vet Clin North Am Small Anim Pract 2006; 36:1107-1127.